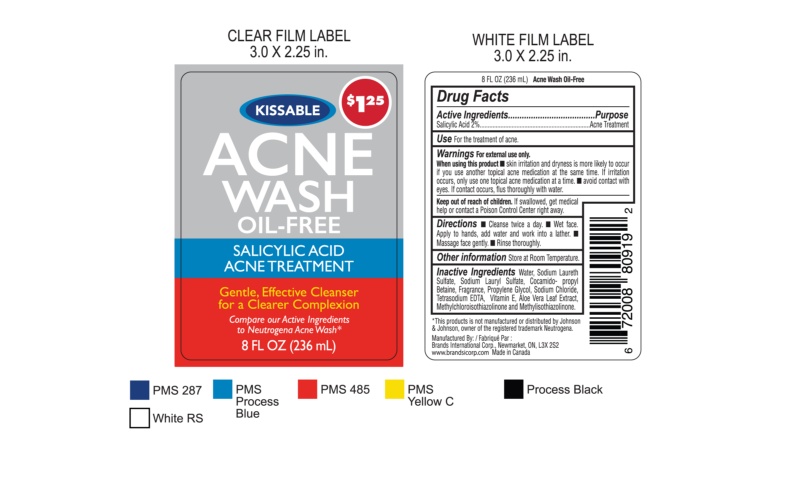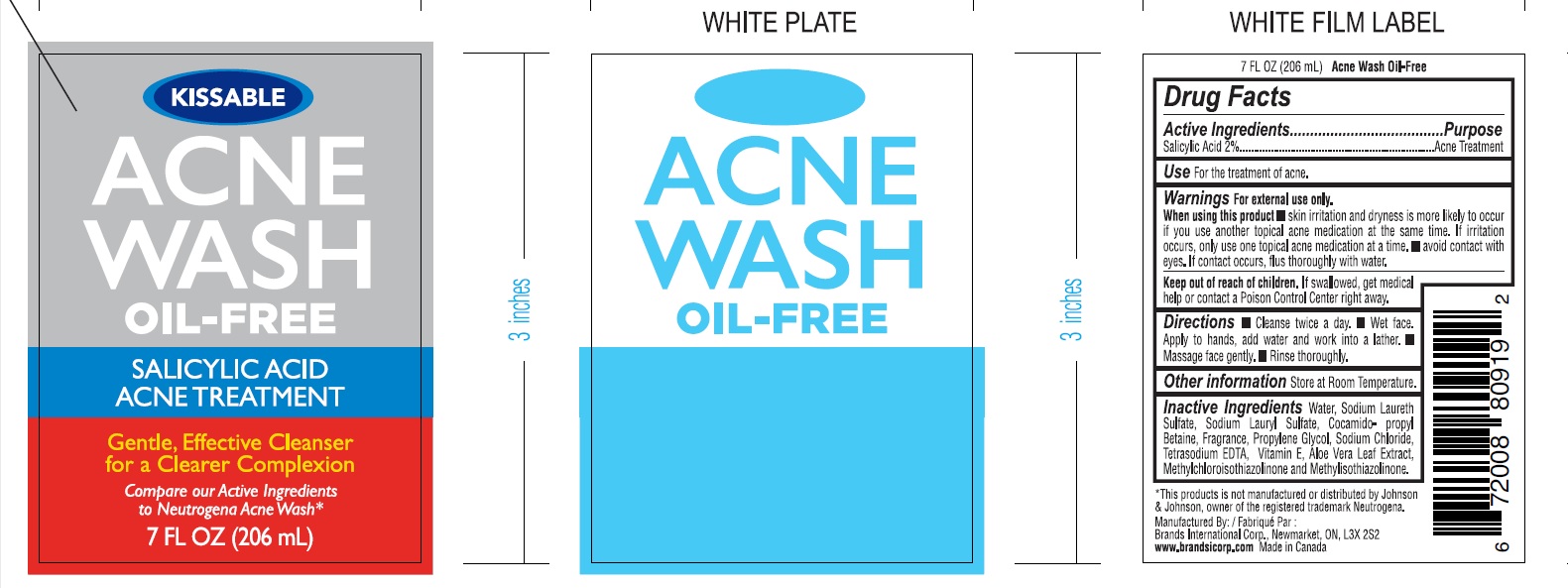 DRUG LABEL: Acne Wash
NDC: 50157-012 | Form: GEL
Manufacturer: BRANDS INTERNATIONAL
Category: otc | Type: HUMAN OTC DRUG LABEL
Date: 20240426

ACTIVE INGREDIENTS: SALICYLIC ACID 2 mg/100 mL
INACTIVE INGREDIENTS: WATER; SODIUM LAURETH SULFATE; COCAMIDOPROPYL BETAINE; SODIUM LAURYL SULFATE; GLYCERIN; ALOE VERA LEAF; METHYLCHLOROISOTHIAZOLINONE; METHYLISOTHIAZOLINONE; SODIUM CHLORIDE; PROPYLENE GLYCOL

Kissable Acne Wash Oil Free

Active Ingredient Purpose

Salicylic Acid 2% ............Acne Treatment

PURPOSE

for the treatment of Acne

Keep out of reach of children. If swallowed, get medical help or contact a Poison Control Center right away.

INDICATIONS AND USAGE

For treatment of acne

DOSAGE AND ADMINISTRATION

Clean twice a day

Wet face, apply to hands add water and work into a lather

Massage fae gently

Rinse thoroughly

WARNINGS

Warning: for external use only.

Ask a doctor or pharmacist before use if you are using other topical acne medications at the same time or immediately following use of this product. This may increase dryness or irritation of the skin. If this occurs, only one medication should be used unless directed by a doctor.

When using this product avoid contact with eyes. If contact occurs, flush thoroughly with water.

OTHER SAFETY INFORMATION

Store at room temparture

INACTIVE INGREDIENT

Inactive Ingredients:water, cocamidopropyl betaine, propylene glycol, sodium chloride, fragrance, Tetra sodium EDTA, aloe barbadensis leaf extract, methylchloroisothiazolinone, methylisothiazoline,